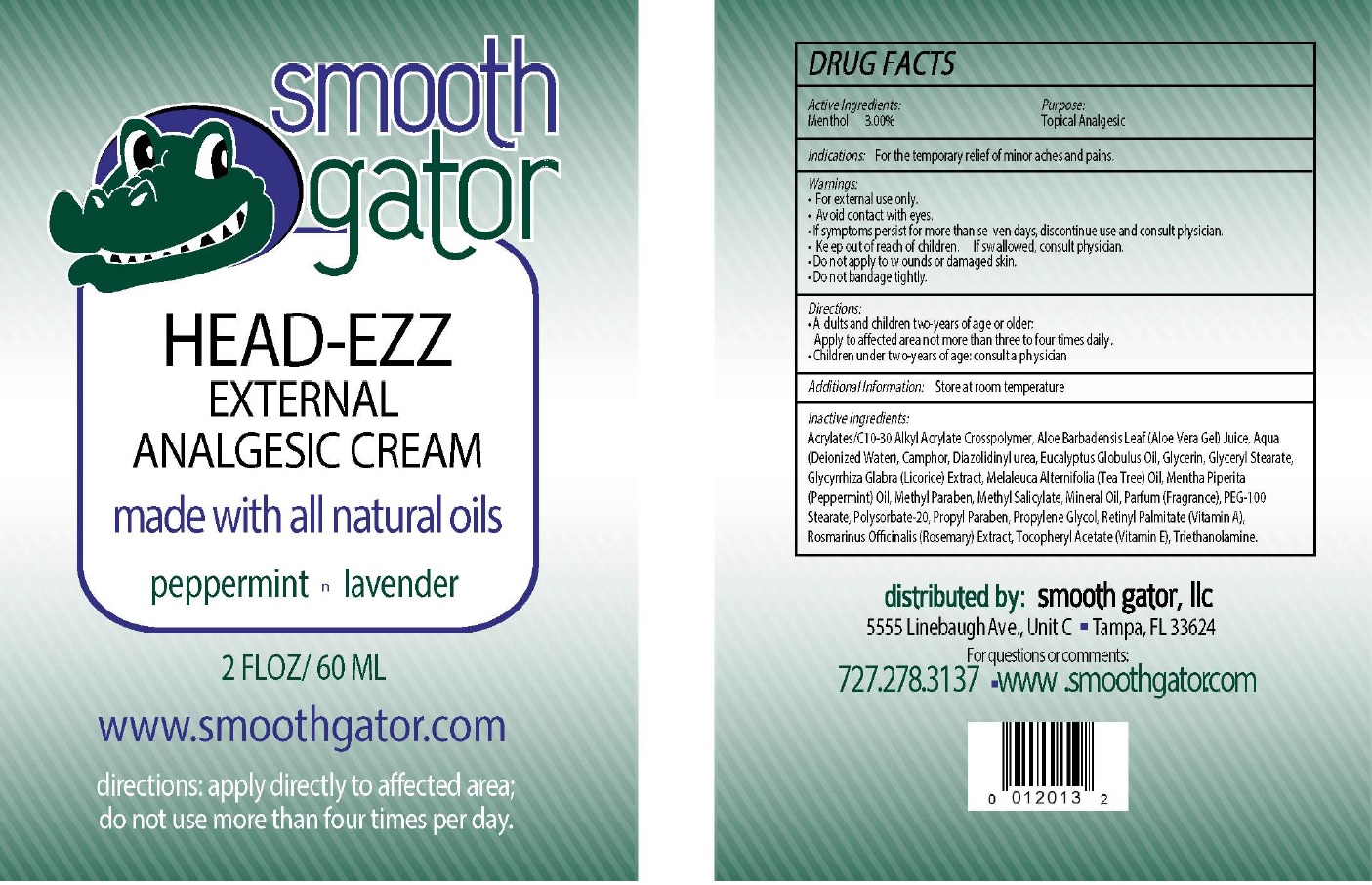 DRUG LABEL: SMOOTH GATOR Head-Ezz Analgesic
NDC: 70673-501 | Form: CREAM
Manufacturer: Smooth Gator LLC
Category: otc | Type: HUMAN OTC DRUG LABEL
Date: 20240610

ACTIVE INGREDIENTS: MENTHOL 30 mg/1 mL
INACTIVE INGREDIENTS: ALOE VERA LEAF; WATER; DIAZOLIDINYL UREA; EUCALYPTUS OIL; GLYCERIN; GLYCERYL MONOSTEARATE; LICORICE; MELALEUCA ALTERNIFOLIA LEAF; PEPPERMINT OIL; METHYLPARABEN; METHYL SALICYLATE; MINERAL OIL; PEG-100 STEARATE; POLYSORBATE 20; PROPYLPARABEN; PROPYLENE GLYCOL; .ALPHA.-TOCOPHEROL; ROSEMARY; TROLAMINE

SMOOTH GATOR Head-Ezz Topical Analgesic Cream

Active Ingredients:

Menthol 3.00%

Purpose

Topical Analgesic

Indications:

For the temporary relief of minor aches and pains.

Warnings

- For external use only.
- Avoid contact with eyes.
- If symptoms persist for more than seven days, discontinue use and consult physician.

Keep out of reach of children.

- If swallowed, consult physician.
- Do not apply to wounds or damaged skin.
- Do not bandage tightly.

Directions:

- Adults and children two-years of age or older: Apply to affected area not more than three to four times daily.
- Children under two-years of age: consult a physician

Additional Information:

Store at room temperature

Inactive Ingredients:

Acrylates/C10-30 Alkyl Acrylate Crosspolymer, Aloe Barbadensis Leaf (Aloe Vera Gel) Juice, Aqua (Deionized Water), Camphor, Diazolidinyl Urea, Eucalyptus Globulus Oil, Glycerin, Glyceryl Stearate, Glycyrrhiza Glabra (Licorice) Extract, Melaleuca Alternifolia (Tea Tree) Oil, Mentha Piperita (Peppermint) Oil, Methyl Paraben, Methyl Salicylate, Mineral Oil, Parfum (Fragrance), PEG-100 Stearate, Polysorbate-20, Propyl Paraben, Propylene Glycol, Retinyl Palmitate (Vitamin E), Rosmarinus Officinalis (Rosemary) Extract, Tocopheryl Acetate (Vitamine E), Triethanolamine.